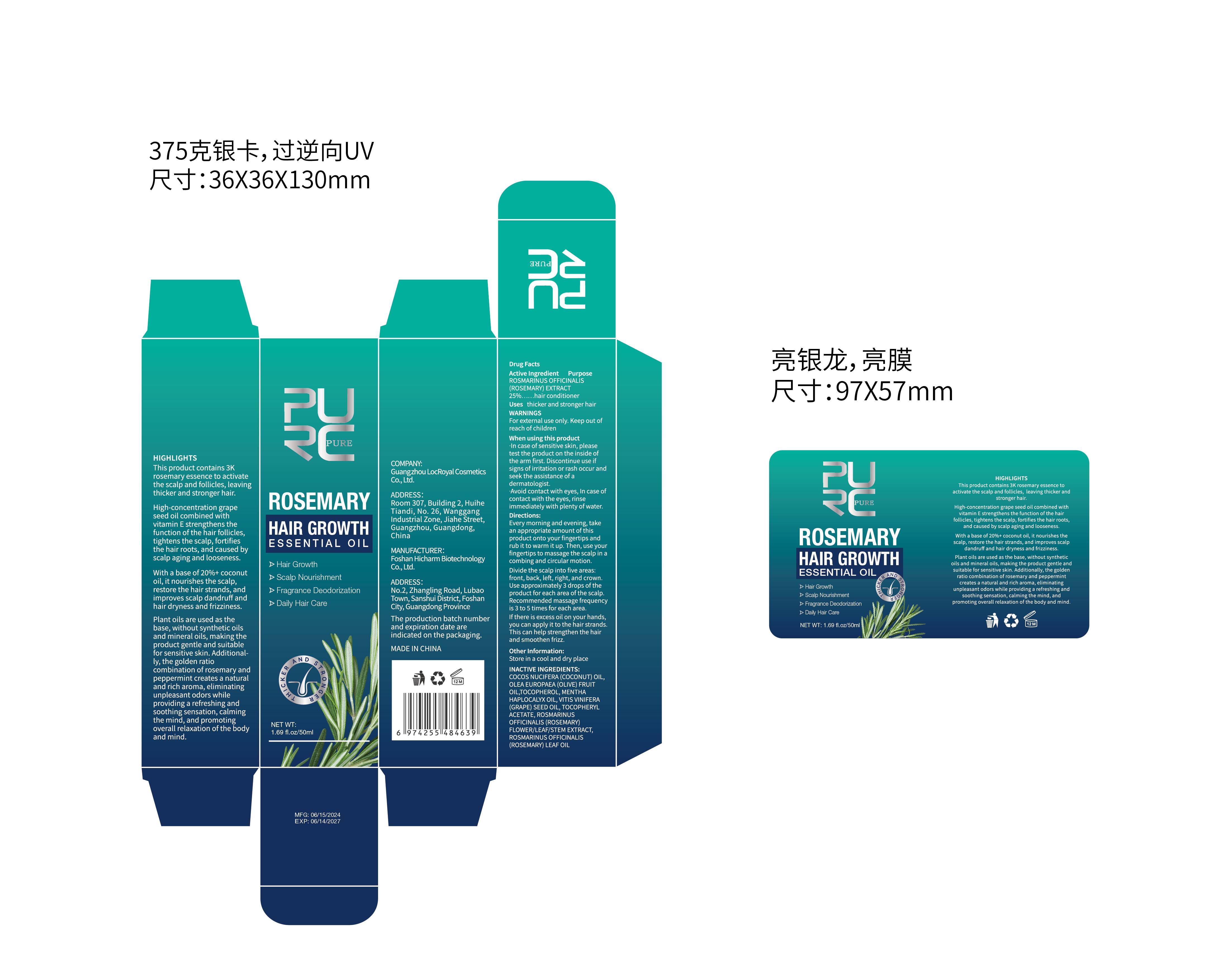 DRUG LABEL: PURC HAIR GROWTH
NDC: 84186-020 | Form: LIQUID
Manufacturer: Guangzhou Bonnieco Cosmetics Co., Ltd
Category: otc | Type: HUMAN OTC DRUG LABEL
Date: 20240708

ACTIVE INGREDIENTS: OLEA EUROPAEA LEAF 25 g/100 mL
INACTIVE INGREDIENTS: COCONUT OIL; .ALPHA.-TOCOPHEROL ACETATE; ROSMARINUS OFFICINALIS FLOWER; GRAPE SEED OIL; MENTHA ARVENSIS TOP; HAPLOPHYLLINE; ROSEMARY OIL

84186-020

Active Ingredient

ROSMARINUS OFFICINALIS (ROSEMARY)EXTRACT 25%

Purpose

Hair Growth
Scalp Nourishment
Fragrance Deodorization
Daily Hair Care

Use

thicker and stronger hair

Warnings

For external use only. Keep out of reach of children

When Using

In case of contact with the eyes, rinse immediately with plenty of water.

Stop Use

If discomfort arises, please immediately stop using the product and seek the assistance of a dermatologist.

Ask Doctor

If discomfort arises, please immediately stop using the product and seek the assistance of a dermatologist.

Keep Oot Of Reach Of Children

Directions

Every morning and evening, takean appropriate amount of thisproduct onto your fingertips andrub it to warm it up. Then, use yourfingertips to massage the scalp in acombing and circular motion.Divide the scalp into five areas:front, back, left, right, and crown.Use approximately 3 drops of theproduct for each area of the scalpRecommended massage frequencyis 3 to 5 times for each area.If there is excess oil on your handsyou can apply it to the hair strands.This can help strengthen the hairand smoothen frizz

Other information

Store in a cool and dry place

Inactive ingredients

COCOS NUCIFERA (COCONUT)OIL,
OLEA EUROPAEA (OLIVE)FRUIT
OILTOCOPHEROL, MENTHA
HAPLOCALYX OIL, VITIS WINIFERA
(GRAPE) SEED OIL,TOCOPHERYL
ACETATE,ROSMARINUS
OFFICINALIS (ROSEMARY)
FLOWER,LEAF/STEM EXTRACT,
ROSMARINUS OFFICINALIS
(ROSEMARY) LEAF OIL